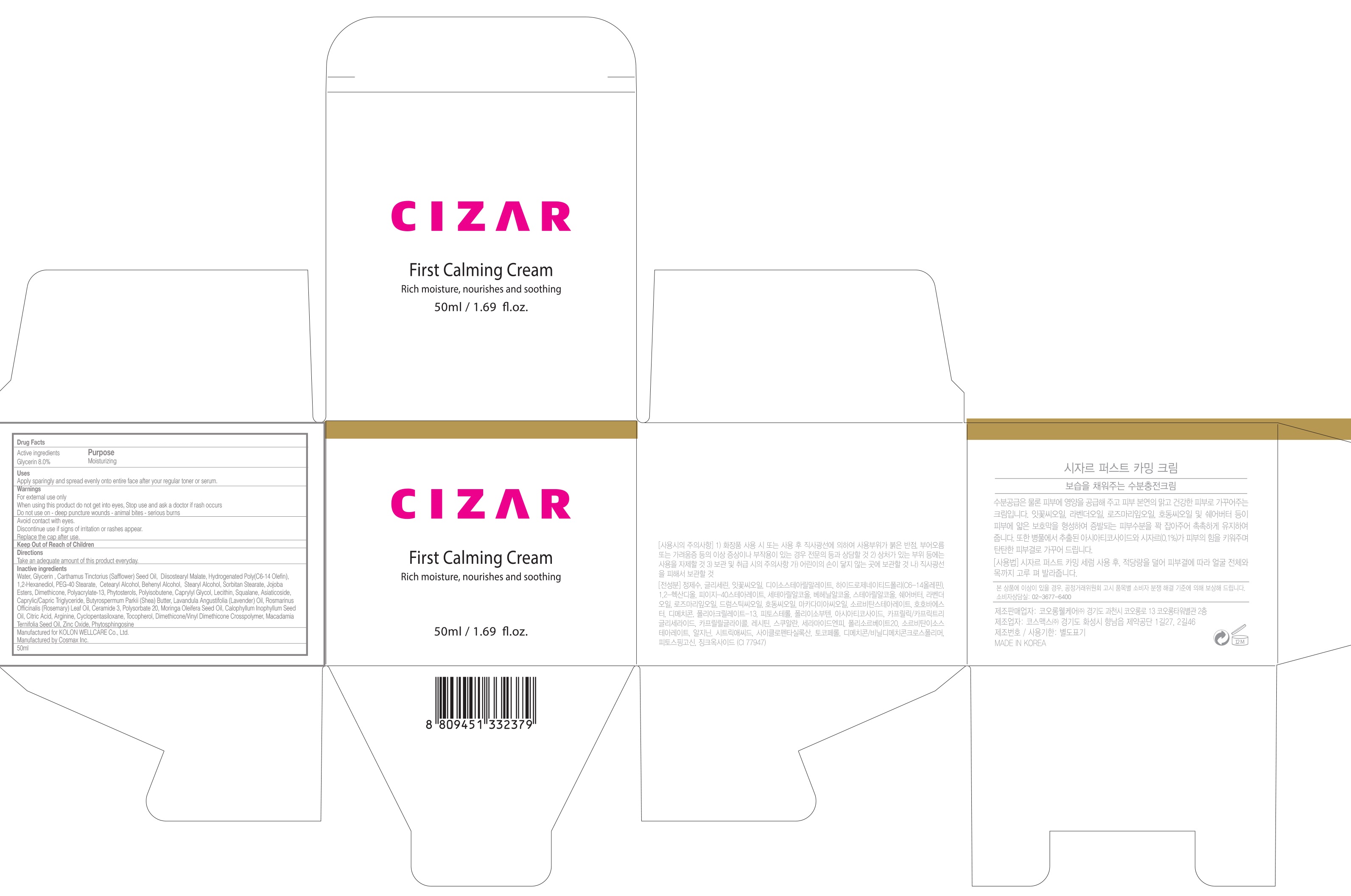 DRUG LABEL: CIZAR First Calming
NDC: 71128-030 | Form: CREAM
Manufacturer: Tissuegene,inc
Category: otc | Type: HUMAN OTC DRUG LABEL
Date: 20181217

ACTIVE INGREDIENTS: Glycerin 4.0 g/50 mL
INACTIVE INGREDIENTS: Water; Diisostearyl Malate

ACTIVE INGREDIENT

Active ingredients: Glycerin 8.0%

INACTIVE INGREDIENT

Inactive ingredients: Water, Carthamus Tinctorius (Safflower) Seed Oil, Diisostearyl Malate, Hydrogenated Poly(C6-14 Olefin), 1,2-Hexanediol, PEG-40 Stearate, Cetearyl Alcohol, Behenyl Alcohol, Stearyl Alcohol, Sorbitan Stearate, Jojoba Esters, Dimethicone, Polyacrylate-13, Phytosterols, Polyisobutene, Caprylyl Glycol, Lecithin, Squalane, Asiaticoside, Caprylic/Capric Triglyceride, Butyrospermum Parkii (Shea) Butter, Lavandula Angustifolia (Lavender) Oil, Rosmarinus Officinalis (Rosemary) Leaf Oil, Ceramide 3, Polysorbate 20, Moringa Oleifera Seed Oil, Calophyllum Inophyllum Seed Oil, Citric Acid, Arginine, Cyclopentasiloxane, Tocopherol, Dimethicone/Vinyl Dimethicone Crosspolymer, Macadamia Ternifolia Seed Oil, Zinc Oxide, Phytosphingosine

PURPOSE

Purpose: Moisturizing

WARNINGS

For external use only When using this product do not get into eyes, Stop use and ask a doctor if rash occurs Do not use on - deep puncture wounds - animal bites - serious burns

Avoid contact with eyes. Discontinue use if signs of irritation or rashes appear. Replace the cap after use. Keep Out of Reach of Children

KEEP OUT OF REACH OF CHILDREN

Uses

Uses: Apply sparingly and spread evenly onto entire face after your regular toner or serum.

Directions

Directions: Take an adequate amount of this product everyday.